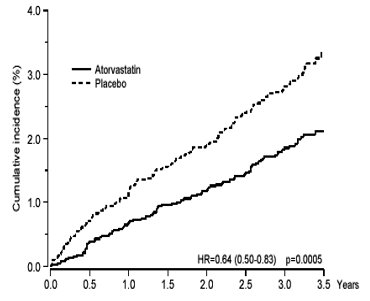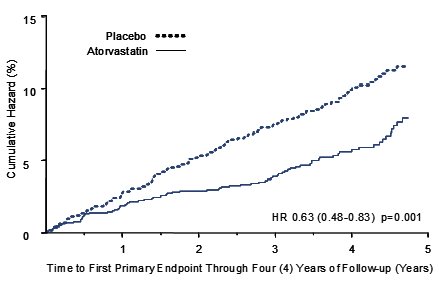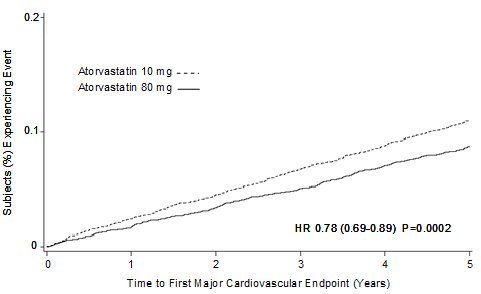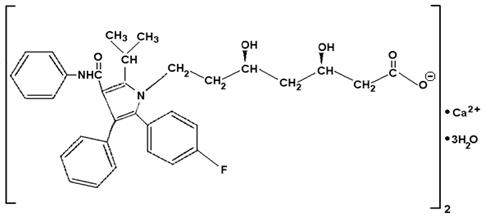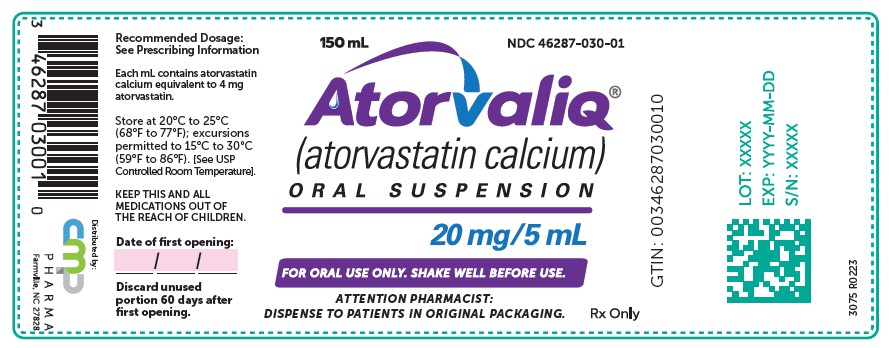 DRUG LABEL: ATORVALIQ
NDC: 46287-030 | Form: Suspension
Manufacturer: CMP Pharma, Inc.
Category: prescription | Type: HUMAN PRESCRIPTION DRUG LABEL
Date: 20240427

ACTIVE INGREDIENTS: ATORVASTATIN CALCIUM TRIHYDRATE 20 mg/5 mL
INACTIVE INGREDIENTS: CARBOXYMETHYLCELLULOSE SODIUM, UNSPECIFIED FORM; MAGNESIUM ALUMINUM SILICATE; METHYLPARABEN; ETHYLPARABEN; PROPYLPARABEN; SUCRALOSE; ACESULFAME POTASSIUM; WATER

HIGHLIGHTS OF PRESCRIBING INFORMATION

These highlights do not include all the information needed to use ATORVALIQ safely and effectively. See full prescribing information for ATORVALIQ.
ATORVALIQ® (atorvastatin calcium) oral suspension
Initial U.S. Approval: 1996

1 INDICATIONS AND USAGE

ATORVALIQ is an HMG-CoA reductase inhibitor (statin) indicated (1):

- To reduce the risk of:
  - Myocardial infarction (MI), stroke, revascularization procedures, and angina in adults with multiple risk factors for coronary heart disease (CHD) but without clinically evident CHD.
  - MI and stroke in adults with type 2 diabetes mellitus with multiple risk factors for CHD but without clinically evident CHD.
  - Non-fatal MI, fatal and non-fatal stroke, revascularization procedures, congestive heart failure (CHF), and angina in adults with clinically evident CHD.
- As an adjunct to diet to reduce low-density lipoprotein (LDL-C) in:
  - Adults with primary hyperlipidemia.
  - Adults and pediatric patients aged 10 years and older with heterozygous familial hypercholesterolemia (HeFH).
- As an adjunct to other LDL-C-lowering therapies to reduce LDL-C in adults and pediatric patients aged 10 years and older with homozygous familial hypercholesterolemia.
- As an adjunct to diet for the treatment of adults with:
  - Primary dysbetaliproteinemia.
  - Hypertriglyceridemia.

2 DOSAGE AND ADMINISTRATION

- Take orally once daily, only on an empty stomach (2.1).
- Assess LDL-C when clinically appropriate, as early as 4 weeks after initiating ATORVALIQ, and adjust dosage if necessary (2.1).
- Adults (2.2):
  - Recommended starting dosage is 10 or 20 mg once daily; dosage range is 10 mg to 80 mg once daily.
  - Patients requiring LDL-C reduction >45% may start at 40 mg once daily.
- Pediatric Patients Aged 10 Years of Age and Older with HeFH: Recommended starting dosage is 10 mg once daily; dosage range is 10 to 20 mg once daily (2.3).
- Pediatric Patients Aged 10 Years of Age and Older with HoFH: Recommended starting dosage is 10 to 20 mg once daily; dosage range is 10 to 80 mg once daily (2.4).
- See full prescribing information for ATORVALIQ dosage modifications due to drug interactions (2.5).

3 DOSAGE FORMS AND STRENGTHS

Oral suspension: 20 mg/5mL (3).

4 CONTRAINDICATIONS

- Acute liver failure or decompensated cirrhosis (4).
- Hypersensitivity to atorvastatin or any excipient in ATORVALIQ (4).

5 WARNINGS AND PRECAUTIONS

- Myopathy and Rhabdomyolysis: Risk factors include age 65 years or greater, uncontrolled hypothyroidism, renal impairment, concomitant use with certain other drugs, and higher ATORVALIQ dosage. Discontinue ATORVALIQ if markedly elevated CK levels occur or myopathy is diagnosed or suspected. Temporarily discontinue ATORVALIQ in patients experiencing an acute or serious condition at high risk of developing renal failure secondary to rhabdomyolysis. Inform patients of the risk of myopathy and rhabdomyolysis when starting or increasing ATORVALIQ dosage. Instruct patients to promptly report unexplained muscle pain, tenderness, or weakness, particularly if accompanied by malaise or fever (2.5, 5.1, 7.1, 8.5, 8.6).
- Immune-Mediated Necrotizing Myopathy (IMNM): Rare reports of IMNM, an autoimmune myopathy, have been reported with statin use. Discontinue ATORVALIQ if IMNM is suspected (5.2).
- Hepatic Dysfunction: Increases in serum transaminases have occurred, some persistent. Rare reports of fatal and non-fatal hepatic failure have occurred. Consider testing liver enzymes before initiating therapy and as clinically indicated thereafter. If serious hepatic injury with clinical symptoms and/or hyperbilirubinemia or jaundice occurs, promptly discontinue ATORVALIQ (5.3).

6 ADVERSE REACTIONS

Most common adverse reactions (incidence ≥5%) are nasopharyngitis, arthralgia, diarrhea, pain in extremity, and urinary tract infection (6.1).

To report SUSPECTED ADVERSE REACTIONS, contact CMP Pharma, Inc. at 1-844-321-1443, or FDA at 1-800-FDA-1088 or www.fda.gov/medwatch.

7 DRUG INTERACTIONS

- See full prescribing information for details regarding concomitant use of ATORVALIQ with other drugs or grapefruit juice that increase the risk of myopathy and rhabdomyolysis (2.5, 7.1).
- Rifampin: May reduce atorvastatin plasma concentrations. Administer simultaneously with ATORVALIQ (7.2).
- Oral Contraceptives: May increase plasma levels of norethindrone and ethinyl estradiol; consider this effect when selecting an oral contraceptive (7.3).
- Digoxin: May increase digoxin plasma levels; monitor patients appropriately (7.3).

8 USE IN SPECIFIC POPULATIONS

- Pregnancy: May cause fetal harm. (8.1).
- Lactation: Breastfeeding not recommended during treatment with ATORVALIQ (8.2).

FULL PRESCRIBING INFORMATION

1 INDICATIONS AND USAGE

ATORVALIQ is indicated:

- To reduce the risk of:
  - Myocardial infarction (MI), stroke, revascularization procedures, and angina in adults with multiple risk factors for coronary heart disease (CHD) but without clinically evident CHD.
  - MI and stroke in adults with type 2 diabetes mellitus with multiple risk factors for CHD but without clinically evident CHD.
  - Non-fatal MI, fatal and non-fatal stroke, revascularization procedures, hospitalization for congestive heart failure, and angina in adults with clinically evident CHD.
- As an adjunct to diet to reduce low-density lipoprotein cholesterol (LDL-C) in:
  - Adults with primary hyperlipidemia.
  - Adults and pediatric patients aged 10 years and older with heterozygous familial hypercholesterolemia (HeFH).
- As an adjunct to other LDL-C-lowering therapies, or alone if such treatments are unavailable, to reduce LDL-C in adults and pediatric patients aged 10 years and older with homozygous familial hypercholesterolemia (HoFH).
- As an adjunct to diet for the treatment of adults with:
  - Primary dysbetalipoproteinemia.
  - Hypertriglyceridemia.

2 DOSAGE AND ADMINISTRATION

2.1 Important Dosage and Administration Information

- Measure the ATORVALIQ dose using a calibrated oral syringe or other oral dosing device scored using metric units of measurements (i.e., mL).
- Take ATORVALIQ orally once daily at any time of day, only on an empty stomach (1 hour before or 2 hours after a meal).
- Advise patients to take a missed dose as soon as possible. If the dose was missed by more than 12 hours, patients should not take the missed dose and resume with the next scheduled dose.
- Assess LDL-C when clinically appropriate, as early as 4 weeks after initiating ATORVALIQ, and adjust the dosage if necessary.

2.2 Recommended Dosage in Adult Patients

The recommended starting dose of ATORVALIQ is 10 mg to 20 mg once daily. The dosage range is 10 mg to 80 mg once daily. Patients who require reduction in LDL-C greater than 45% may be started at 40 mg once daily.

2.3 Recommended Dosage in Pediatric Patients 10 Years of Age and Older with HeFH

The recommended starting dosage of ATORVALIQ is 10 mg once daily. The dosage range is 10 mg to 20 mg once daily.

2.4 Recommended Dosage in Pediatric Patients 10 Years of Age and Older with HoFH

The recommended starting dosage of ATORVALIQ is 10 mg to 20 mg once daily. The dosage range is 10 mg to 80 mg once daily.

2.5 Dosage Modifications Due to Drug Interactions

Concomitant use of ATORVALIQ with the following drugs requires dosage modification of ATORVALIQ [see Warnings and Precautions (5.1) and Drug Interactions (7.1)].

Anti-Viral Medications

- In patients taking saquinavir plus ritonavir, darunavir plus ritonavir, fosamprenavir, fosamprenavir plus ritonavir, elbasvir plus grazoprevir or letermovir, do not exceed ATORVALIQ 20 mg once daily.
- In patients taking nelfinavir, do not exceed ATORVALIQ 40 mg once daily.

Select Azole Antifungals or Macrolide Antibiotics

- In patients taking clarithromycin or itraconazole, do not exceed ATORVALIQ 20 mg once daily.

For additional recommendations regarding concomitant use of ATORVALIQ with other anti-viral medications, azole antifungals or macrolide antibiotics, [see Drug Interactions (7.1)].

3 DOSAGE FORMS AND STRENGTHS

Oral Suspension: 20 mg/5mL white to off-white suspension with an orange flavor.

4 CONTRAINDICATIONS

ATORVALIQ is contraindicated in patients with:

- Acute liver failure or decompensated cirrhosis [see Warnings and Precautions (5.3)]
- Hypersensitivity to atorvastatin or any excipients in ATORVALIQ. Hypersensitivity reactions, including anaphylaxis, angioneurotic edema, erythema multiforme, Stevens-Johnson syndrome, and toxic epidermal necrolysis, have been reported [see Adverse Reactions (6.2)].

5 WARNINGS AND PRECAUTIONS

5.1 Myopathy and Rhabdomyolysis

ATORVALIQ may cause myopathy (muscle pain, tenderness, or weakness associated with elevated creatine kinase [CK]) and rhabdomyolysis. Acute kidney injury secondary to myoglobinuria and rare fatalities have occurred as a result of rhabdomyolysis in patients treated with statins, including ATORVALIQ.

Risk factors for myopathy include age 65 years or greater, uncontrolled hypothyroidism, renal impairment, concomitant use with certain other drugs (including other lipid-lowering therapies), and higher ATORVALIQ dosage [see Drug Interactions (7.1) and Use in Specific Populations (8.5, 8.6)].

Steps to Prevent or Reduce the Risk of Myopathy and Rhabdomyolysis

ATORVALIQ exposure may be increased by drug interactions due to inhibition of cytochrome P450 enzyme 3A4 (CYP3A4) and/or transporters (e.g., breast cancer resistant protein [BCRP], organic anion-transporting polypeptide [OATP1B1/OATP1B3] and P-glycoprotein [P-gp]), resulting in an increased risk of myopathy and rhabdomyolysis. Concomitant use of cyclosporine, gemfibrozil, tipranavir plus ritonavir, or glecaprevir plus pibrentasvir with ATORVALIQ is not recommended. ATORVALIQ dosage modifications are recommended for patients taking certain anti-viral, azole antifungals, or macrolide antibiotic medications [see Dosage and Administration (2.5)]. Cases of myopathy/rhabdomyolysis have been reported with atorvastatin co-administered with lipid modifying doses (>1 gram/day) of niacin, fibrates, colchicine, and ledipasvir plus sofosbuvir [see Adverse Reactions (6.1)]. Consider if the benefit of use of these products outweighs the increased risk of myopathy and rhabdomyolysis [see Drug Interactions (7.1)].

Concomitant intake of large quantities, more than 1.2 liters daily, of grapefruit juice is not recommended in patients taking ATORVALIQ [see Drug Interactions (7.1)].

Discontinue ATORVALIQ if markedly elevated CK levels occur or if myopathy is either diagnosed or suspected. Muscle symptoms and CK elevations may resolve if ATORVALIQ is discontinued. Temporarily discontinue ATORVALIQ in patients experiencing an acute or serious condition at high risk of developing renal failure secondary to rhabdomyolysis (e.g., sepsis; shock; severe hypovolemia; major surgery; trauma; severe metabolic, endocrine, or electrolyte disorders; or uncontrolled epilepsy).

Inform patients of the risk of myopathy and rhabdomyolysis when starting or increasing the ATORVALIQ dosage. Instruct patients to promptly report any unexplained muscle pain, tenderness or weakness, particularly if accompanied by malaise or fever.

5.2 Immune-Mediated Necrotizing Myopathy

There have been rare reports of immune-mediated necrotizing myopathy (IMNM), an autoimmune myopathy, associated with statin use, including reports of recurrence when the same or different statin was administered. IMNM is characterized by proximal muscle weakness and elevated serum creatine kinase that persists despite discontinuation of statin treatment; positive anti-HMG CoA reductase antibody; muscle biopsy showing necrotizing myopathy; and improvement with immunosuppressive agents. Additional neuromuscular and serologic testing may be necessary. Treatment with immunosuppressive agents may be required. Discontinue ATORVALIQ if IMNM is suspected.

5.3 Hepatic Dysfunction

Increases in serum transaminases have been reported with use of atorvastatin [see Adverse Reactions (6.1)]. In most cases, these changes appeared soon after initiation, were transient, were not accompanied by symptoms, and resolved or improved on continued therapy or after a brief interruption in therapy. Persistent increases to more than three times the ULN in serum transaminases have occurred in approximately 0.7% of patients receiving atorvastatin in clinical trials. There have been rare postmarketing reports of fatal and non-fatal hepatic failure in patients taking statins, including atorvastatin.

Patients who consume substantial quantities of alcohol and/or have a history of liver disease may be at increased risk for hepatic injury [see Use in Specific Populations (8.7)].

Consider liver enzyme testing before ATORVALIQ initiation and when clinically indicated thereafter. ATORVALIQ is contraindicated in patients with acute liver failure or decompensated cirrhosis [see Contraindications (4)]. If serious hepatic injury with clinical symptoms and/or hyperbilirubinemia or jaundice occurs, promptly discontinue ATORVALIQ.

5.4 Increases in HbA1c and Fasting Serum Glucose Levels

Increases in HbA1c and fasting serum glucose levels have been reported with statins, including atorvastatin. Optimize lifestyle measures, including regular exercise, maintaining a healthy body weight, and making healthy food choices.

5.5 Increased Risk of Hemorrhagic Stroke in Patients on Atorvastatin 80 mg with Recent Hemorrhagic Stroke

In a post-hoc analysis of the Stroke Prevention by Aggressive Reduction in Cholesterol Levels (SPARCL) trial where 2,365 adult patients, without CHD who had a stroke or TIA within the preceding 6 months, were treated with atorvastatin 80 mg, a higher incidence of hemorrhagic stroke was seen in the atorvastatin 80 mg group compared to placebo (55, 2.3% ATORVALIQ vs. 33, 1.4% placebo; HR: 1.68, 95% CI: 1.09, 2.59; p=0.0168). The incidence of fatal hemorrhagic stroke was similar across treatment groups (17 vs. 18 for the atorvastatin and placebo groups, respectively). The incidence of non-fatal hemorrhagic stroke was significantly higher in the atorvastatin group (38, 1.6%) as compared to the placebo group (16, 0.7%). Some baseline characteristics, including hemorrhagic and lacunar stroke on study entry, were associated with a higher incidence of hemorrhagic stroke in the atorvastatin group [see Adverse Reactions (6.1)]. Consider the risk/benefit of use of ATORVALIQ 80 mg in patients with recent hemorrhagic stroke.

6 ADVERSE REACTIONS

The following important adverse reactions are described below and elsewhere in the labeling:

- Myopathy and Rhabdomyolysis [see Warnings and Precautions (5.1)]
- Immune-Mediated Necrotizing Myopathy [see Warnings and Precautions (5.2)]
- Hepatic Dysfunction [see Warnings and Precautions (5.3)]
- Increases in HbA1c and Fasting Serum Glucose Levels [see Warnings and Precautions (5.4)]

6.1 Clinical Trials Experience

Because clinical trials are conducted under widely varying conditions, the adverse reaction rates observed in the clinical trials of a drug cannot be directly compared to rates in the clinical trials of another drug and may not reflect the rates observed in practice.

The safety of ATORVALIQ has been established in adequate and well-controlled trials of atorvastatin calcium tablets, referenced below as “atorvastatin” [see Clinical Studies (14)].

In the atorvastatin placebo-controlled clinical trial database of 16,066 patients (8,755 atorvastatin vs. 7,311 placebo; age range 10-93 years, 39% women, 91% White, 3% Black, 2% Asian, 4% other) with a median treatment duration of 53 weeks, the most common adverse reactions in patients treated with atorvastatin that led to treatment discontinuation and occurred at a rate greater than placebo were: myalgia (0.7%), diarrhea (0.5%), nausea (0.4%), alanine aminotransferase increase (0.4%), and hepatic enzyme increase (0.4%).

Table 1 summarizes adverse reactions reported in ≥ 2% and at a rate greater than placebo in patients treated with atorvastatin (n=8,755), from seventeen placebo-controlled trials.

Table 1: Adverse Reactions Occurring in ≥ 2% in Patients Atorvastatin-Treated with any Dose and Greater than Placebo
Adverse Reaction | % Placebo N=7,311 | % 10 mg N=3908 | % 20 mg N=188 | % 40 mg N=604 | % 80 mg N=4055 | % Any dose N=8,755
Nasopharyngitis | 8.2 | 12.9 | 5.3 | 7.0 | 4.2 | 8.3
Arthralgia | 6.5 | 8.9 | 11.7 | 10.6 | 4.3 | 6.9
Diarrhea | 6.3 | 7.3 | 6.4 | 14.1 | 5.2 | 6.8
Pain in extremity | 5.9 | 8.5 | 3.7 | 9.3 | 3.1 | 6.0
Urinary tract infection | 5.6 | 6.9 | 6.4 | 8.0 | 4.1 | 5.7
Dyspepsia | 4.3 | 5.9 | 3.2 | 6.0 | 3.3 | 4.7
Nausea | 3.5 | 3.7 | 3.7 | 7.1 | 3.8 | 4.0
Musculoskeletal pain | 3.6 | 5.2 | 3.2 | 5.1 | 2.3 | 3.8
Muscle spasms | 3.0 | 4.6 | 4.8 | 5.1 | 2.4 | 3.6
Myalgia | 3.1 | 3.6 | 5.9 | 8.4 | 2.7 | 3.5
Insomnia | 2.9 | 2.8 | 1.1 | 5.3 | 2.8 | 3.0
Pharyngolaryngeal pain | 2.1 | 3.9 | 1.6 | 2.8 | 0.7 | 2.3

Other adverse reactions reported in placebo-controlled studies include:

Body as a whole: malaise, pyrexia

Digestive system: abdominal discomfort, eructation, flatulence, hepatitis, cholestasis

Musculoskeletal system: musculoskeletal pain, muscle fatigue, neck pain, joint swelling

Metabolic and nutritional system: transaminases increase, liver function test abnormal, blood alkaline phosphatase increase, creatine phosphokinase increase, hyperglycemia

Nervous system: nightmare

Respiratory system: epistaxis

Skin and appendages: urticaria

Special senses: vision blurred, tinnitus

Urogenital system: white blood cells urine positive

Elevations in Liver Enzyme Tests

Persistent elevations in serum transaminases, defined as more than 3 times the ULN and occurring on 2 or more occasions, occurred in 0.7% of patients who received atorvastatin in clinical trials. The incidence of these abnormalities was 0.2%, 0.2%, 0.6%, and 2.3% for 10, 20, 40, and 80 mg, respectively.

One patient in clinical trials developed jaundice. Increases in liver enzyme tests in other patients were not associated with jaundice or other clinical signs or symptoms. Upon dose reduction, drug interruption, or discontinuation, transaminase levels returned to or near pretreatment levels without sequelae. Eighteen of 30 patients with persistent liver enzyme elevations continued treatment with a reduced dose of atorvastatin.

Treating to New Targets Study (TNT)

In TNT, [see Clinical Studies (14.1)] 10,001 patients (age range 29-78 years, 19% women; 94% White, 3% Black, 1% Asian, 2% other) with clinically evident CHD were treated with atorvastatin 10 mg daily (n=5,006) or atorvastatin 80 mg daily (n=4,995). In the high-dose atorvastatin group, there were more patients with serious adverse reactions (1.8%) and discontinuations due to adverse reactions (9.9%) as compared to the low-dose group (1.4%; 8.1%, respectively) during a median follow-up of 4.9 years. Persistent transaminase elevations (≥3 x ULN twice within 4-10 days) occurred in 1.3% of individuals with atorvastatin 80 mg and in 0.2% of individuals with atorvastatin 10 mg. Elevations of CK (≥ 10 x ULN) were higher in the high-dose atorvastatin group (0.3%) compared to the low-dose atorvastatin group (0.1%).

Stroke Prevention by Aggressive Reduction in Cholesterol Levels (SPARCL)

In SPARCL, 4,731 patients (age range 21-92 years, 40% women; 93% White, 3% Black, 1% Asian, 3% other) without clinically evident CHD but with a stroke or transient ischemic attack (TIA) within the previous 6 months were treated with atorvastatin 80 mg (n=2,365) or placebo (n=2,366) for a median follow-up of 4.9 years. There was a higher incidence of persistent hepatic transaminase elevations (≥ 3 x ULN twice within 4-10 days) in the atorvastatin group (0.9%) compared to placebo (0.1%). Elevations of CK (>10 x ULN) were rare, but were higher in the atorvastatin group (0.1%) compared to placebo (0.0%). Diabetes was reported as an adverse reaction in 6.1% of subjects in the atorvastatin group and 3.8% of subjects in the placebo group.

In a post-hoc analysis, atorvastatin 80 mg reduced the incidence of ischemic stroke (9.2% vs. 11.6%) and increased the incidence of hemorrhagic stroke (2.3% vs. 1.4%) compared to placebo. The incidence of fatal hemorrhagic stroke was similar between groups (17 atorvastatin vs. 18 placebo). The incidence of non-fatal hemorrhagic strokes was significantly greater in the atorvastatin group (38 non-fatal hemorrhagic strokes) as compared to the placebo group (16 non-fatal hemorrhagic strokes). Patients who entered the trial with a hemorrhagic stroke appeared to be at increased risk for hemorrhagic stroke (16% atorvastatin vs. 4% placebo).

Adverse Reactions from Clinical Studies of Atorvastatin in Pediatric Patients with HeFH

In a 26-week controlled study in pediatric patients with HeFH (ages 10 years to 17 years) (n=140, 31% female; 92% White, 1.6% Blacks, 1.6% Asians, 4.8% other), the safety and tolerability profile of atorvastatin 10 to 20 mg daily, as an adjunct to diet to reduce total cholesterol, LDL-C, and apo B levels, was generally similar to that of placebo [see Use in Specific Populations (8.4) and Clinical Studies (14)].

6.2 Postmarketing Experience

The following adverse reactions have been identified during post-approval use of atorvastatin. Because these reactions are reported voluntarily from a population of uncertain size, it is not always possible to reliably estimate their frequency or establish a causal relationship to drug exposure.

Gastrointestinal disorders: pancreatitis

General disorders: fatigue

Hepatobiliary Disorders: fatal and non-fatal hepatic failure

Immune system disorders: anaphylaxis

Injury: tendon rupture

Musculoskeletal and connective tissue disorders: rhabdomyolysis, myositis.

There have been rare reports of immune-mediated necrotizing myopathy associated with statin use.

Nervous system disorders: dizziness, peripheral neuropathy.
There have been rare reports of cognitive impairment (e.g., memory loss, forgetfulness, amnesia, memory impairment, confusion) associated with the use of all statins. Cognitive impairment was generally nonserious, and reversible upon statin discontinuation, with variable times to symptom onset (1 day to years) and symptom resolution (median of 3 weeks).
There have been rare reports of new onset or exacerbation of myasthenia gravis, including ocular myasthenia, and reports of recurrence when the same or a different statin was administered.

Psychiatric disorders: depression

Respiratory disorders: interstitial lung disease

Skin and subcutaneous tissue disorders: angioneurotic edema, bullous rashes (including erythema multiforme, Stevens-Johnson syndrome, and toxic epidermal necrolysis)

7 DRUG INTERACTIONS

7.1 Drug Interactions that may Increase the Risk of Myopathy and Rhabdomyolysis with ATORVALIQ

Atorvastatin is a substrate of CYP3A4 and transporters (e.g., OATP1B1/1B3, P-gp, or BCRP). Atorvastatin plasma levels can be significantly increased with concomitant administration of inhibitors of CYP3A4 and transporters. Table 2 includes a list of drugs that may increase exposure to atorvastatin and may increase the risk of myopathy and rhabdomyolysis when used concomitantly and instructions for preventing or managing them [see Warnings and Precautions (5.1) and Clinical Pharmacology (12.3)].

Table 2: Drug Interactions that may Increase the Risk of Myopathy and Rhabdomyolysis with ATORVALIQ
Cyclosporine or Gemfibrozil
Clinical Impact: | Atorvastatin plasma levels were significantly increased with concomitant administration of atorvastatin and cyclosporine, an inhibitor of CYP3A4 and OATP1B1 [see Clinical Pharmacology (12.3)]. Gemfibrozil may cause myopathy when given alone. The risk of myopathy and rhabdomyolysis is increased with concomitant use of cyclosporine or gemfibrozil with ATORVALIQ.
Intervention: | Concomitant use of cyclosporine or gemfibrozil with ATORVALIQ is not recommended.
Anti-Viral Medications
Clinical Impact: | Atorvastatin plasma levels were significantly increased with concomitant administration of ATORVALIQ with many anti-viral medications, which are inhibitors of CYP3A4 and/or transporters (e.g., BCRP, OATP1B1/1B3, P-gp, MRP2, and/or OAT2) [see Clinical Pharmacology (12.3)]. Cases of myopathy and rhabdomyolysis have been reported with concomitant use of ledipasvir plus sofosbuvir with atorvastatin.
Intervention: | - Concomitant use of tipranavir plus ritonavir or glecaprevir plus pibrentasvir with ATORVALIQ is not recommended. - In patients taking lopinavir plus ritonavir, or simeprevir, consider the risk/benefit of concomitant use with ATORVALIQ. - In patients taking saquinavir plus ritonavir, darunavir plus ritonavir, fosamprenavir, fosamprenavir plus ritonavir, elbasvir plus grazoprevir or letermovir, do not exceed ATORVALIQ 20 mg. - In patients taking nelfinavir, do not exceed ATORVALIQ 40 mg [see Dosage and Administration (2.5)]. - Consider the risk/benefit of concomitant use of ledipasvir plus sofosbuvir with ATORVALIQ. - Monitor all patients for signs and symptoms of myopathy particularly during initiation of therapy and during upward dose titration of either drug.
Examples: | Tipranavir plus ritonavir, glecaprevir plus pibrentasvir, lopinavir plus ritonavir, simeprevir, saquinavir plus ritonavir, darunavir plus ritonavir, fosamprenavir, fosamprenavir plus ritonavir, elbasvir plus grazoprevir, letermovir, nelfinavir, and ledipasvir plus sofosbuvir.
Select Azole Antifungals or Macrolide Antibiotics
Clinical Impact: | Atorvastatin plasma levels were significantly increased with concomitant administration of ATORVALIQ with select azole antifungals or macrolide antibiotics, due to inhibition of CYP3A4 and/or transporters [see Clinical Pharmacology (12.3)].
Intervention: | In patients taking clarithromycin or itraconazole, do not exceed ATORVALIQ 20 mg [see Dosage and Administration (2.5)]. Consider the risk/benefit of concomitant use of other azole antifungals or macrolide antibiotics with ATORVALIQ. Monitor all patients for signs and symptoms of myopathy particularly during initiation of therapy and during upward dose titration of either drug.
Examples: | Erythromycin, clarithromycin, itraconazole, ketoconazole, posaconazole, and voriconazole.
Niacin
Clinical Impact: | Cases of myopathy and rhabdomyolysis have been observed with concomitant use of lipid modifying dosages of niacin (≥1 gram/day niacin) with atorvastatin [see Warnings and Precaustions (5.1)].
Intervention: | Consider if the benefit of using lipid modifying dosages of niacin concomitantly with ATORVALIQ outweighs the increased risk of myopathy and rhabdomyolysis. If concomitant use is decided, monitor patients for signs and symptoms of myopathy particularly during initiation of therapy and during upward dose titration of either drug.
Fibrates (other than Gemfibrozil)
Clinical Impact: | Fibrates may cause myopathy when given alone. The risk of myopathy and rhabdomyolysis is increased with concomitant use of fibrates with ATORVALIQ.
Intervention: | Consider if the benefit of using fibrates concomitantly with ATORVALIQ outweighs the increased risk of myopathy and rhabdomyolysis. If concomitant use is decided, monitor patients for signs and symptoms of myopathy particularly during initiation of therapy and during upward dose titration of either drug.
Colchicine
Clinical Impact: | Cases of myopathy and rhabdomyolysis have been reported with concomitant use of colchicine with atorvastatin.
Intervention: | Consider the risk/benefit of concomitant use of colchicine with ATORVALIQ. If concomitant use is decided, monitor patients for signs and symptoms of myopathy particularly during initiation of therapy and during upward dose titration of either drug.
Grapefruit Juice
Clinical Impact: | Grapefruit juice consumption, especially excessive consumption, more than 1.2 liters/daily, can raise the plasma levels of atorvastatin and may increase the risk of myopathy and rhabdomyolysis.
Intervention: | Avoid intake of large quantities of grapefruit juice, more than 1.2 liters daily, when taking ATORVALIQ.

7.2 Drug Interactions that may Decrease Exposure to ATORVALIQ

Table 3 presents drug interactions that may decrease exposure to ATORVALIQ and instructions for preventing or managing them.

Table 3: Drug Interactions that may Decrease Exposure to ATORVALIQ
Rifampin
Clinical Impact: | Concomitant administration of atorvastatin with rifampin, an inducer of cytochrome P450 3A4 and inhibitor of OATP1B1, can lead to variable reductions in plasma concentrations of atorvastatin. Due to the dual interaction mechanism of rifampin, delayed administration of ATORVALIQ after administration of rifampin has been associated with a significant reduction in atorvastatin plasma concentrations.
Intervention: | Administer ATORVALIQ and rifampin simultaneously.

7.3 ATORVALIQ Effects on Other Drugs

Table 4 presents atorvastatin’s effect on other drugs and instructions for preventing or managing them.

Table 4: ATORVALIQ Effects on Other Drugs
Oral Contraceptives
Clinical Impact: | Co-administration of atorvastatin and an oral contraceptive increased plasma concentrations of norethindrone and ethinyl estradiol [see Clinical Pharmacology (12.3)].
Intervention: | Consider this when selecting an oral contraceptive for patients taking ATORVALIQ.
Digoxin
Clinical Impact: | When multiple doses of atorvastatin and digoxin were co-administered, steady state plasma digoxin concentrations increased [see Clinical Pharmacology (12.3)].
Intervention: | Monitor patients taking digoxin appropriately.

8 USE IN SPECIFIC POPULATIONS

8.1 Pregnancy

Risk Summary

Discontinue ATORVALIQ when pregnancy is recognized. Alternatively, consider the ongoing therapeutic needs of the individual patient. Atorvastatin decreases synthesis of cholesterol and possibly other biologically active substances derived from cholesterol; therefore, ATORVALIQ may cause fetal harm when administered to pregnant patients based on the mechanism of action [see Clinical Pharmacology (12.1)]. In addition, treatment of hyperlipidemia is not generally necessary during pregnancy. Atherosclerosis is a chronic process and the discontinuation of lipid-lowering drugs during pregnancy should have little impact on the outcome of long-term therapy of primary hyperlipidemia for most patients.

Available data from case series and prospective and retrospective observational cohort studies over decades of use with statins in pregnant women have not identified a drug-associated risk of major congenital malformations. Published data from prospective and retrospective observational cohort studies with atorvastatin use in pregnant women are insufficient to determine if there is a drug-associated risk of miscarriage (see Data). In animal reproduction studies, no adverse developmental effects were observed in pregnant rats or rabbits orally administered atorvastatin at doses that resulted in up to 30 and 20 times, respectively, the human exposure at the maximum recommended human dose (MRHD) of 80 mg, based on body surface area (mg/m^2). In rats administered atorvastatin during gestation and lactation, decreased postnatal growth and development delay were observed at doses ≥ 6 times the MRHD (see Data).

The estimated background risk of major birth defects and miscarriage for the indicated population is unknown. In the U.S. general population, the estimated background risk of major birth defects and miscarriage in clinically recognized pregnancies is 2-4% and 15-20%, respectively.

Data

Human Data

A Medicaid cohort linkage study of 1152 statin-exposed pregnant women compared to 886,996 controls did not find a significant teratogenic effect from maternal use of statins in the first trimester of pregnancy, after adjusting for potential confounders – including maternal age, diabetes mellitus, hypertension, obesity, and alcohol and tobacco use – using propensity score-based methods. The relative risk of congenital malformations between the group with statin use and the group with no statin use in the first trimester was 1.07 (95% confidence interval 0.85 to 1.37) after controlling for confounders, particularly pre-existing diabetes mellitus. There were also no statistically significant increases in any of the organ-specific malformations assessed after accounting for confounders. In the majority of pregnancies, statin treatment was initiated prior to pregnancy and was discontinued at some point in the first trimester when pregnancy was identified. Study limitations include reliance on physician coding to define the presence of a malformation, lack of control for certain confounders such as body mass index, use of prescription dispensing as verification for the use of a statin, and lack of information on non-live births.

Animal Data

Atorvastatin was administered to pregnant rats and rabbits during organogenesis at oral doses up to 300 mg/kg/day and 100 mg/kg/day, respectively. Atorvastatin was not teratogenic in rats at doses up to 300 mg/kg/day or in rabbits at doses up to 100 mg/kg/day. These doses resulted in multiples of about 30 times (rat) or 20 times (rabbit) the human exposure at the MRHD based on surface area (mg/m^2). In rats, the maternally toxic dose of 300 mg/kg resulted in increased post-implantation loss and decreased fetal body weight. At the maternally toxic doses of 50 and 100 mg/kg/day in rabbits, there was increased post-implantation loss, and at 100 mg/kg/day fetal body weights were decreased.

In a study in pregnant rats administered 20, 100, or 225 mg/kg/day from gestation day 7 through to lactation day 20 (weaning), there was decreased survival at birth, postnatal day 4, weaning, and post-weaning in pups of mothers dosed with 225 mg/kg/day, a dose at which maternal toxicity was observed. Pup body weight was decreased through postnatal day 21 at 100 mg/kg/day, and through postnatal day 91 at 225 mg/kg/day. Pup development was delayed (rotorod performance at 100 mg/kg/day and acoustic startle at 225 mg/kg/day; pinnae detachment and eye-opening at 225 mg/kg/day). These doses correspond to 6 times (100 mg/kg) and 22 times (225 mg/kg) the human exposure at the MRHD, based on AUC.

Atorvastatin crosses the rat placenta and reaches a level in fetal liver equivalent to that of maternal plasma.

8.2 Lactation

Risk Summary

There is no information about the presence of atorvastatin in human milk, the effects of the drug on the breastfed infant or the effects of the drug on milk production. However, it has been shown that another drug in this class passes into human milk. Studies in rats have shown that atorvastatin and/or its metabolites are present in the breast milk of lactating rats. When a drug is present in animal milk, it is likely that the drug will be present in human milk (see Data). Statins, including ATORVALIQ, decrease cholesterol synthesis and possibly the synthesis of other biologically active substances derived from cholesterol and may cause harm to the breastfed infant. Because of the potential for serious adverse reactions in a breastfed infant, based on the mechanism of action, advise patients that breastfeeding is not recommended during treatment with ATORVALIQ [see Use in Specific Populations (8.1), and Clinical Pharmacology (12.1)].

Data

Following a single oral administration of 10 mg/kg of radioactive atorvastatin to lactating rats, the concentration of total radioactivity was determined. Atorvastatin and/or its metabolites were measured in the breast milk and pup plasma at a 2:1 ratio (milk:plasma).

8.4 Pediatric Use

The safety and effectiveness of ATORVALIQ as an adjunct to diet to reduce LDL-C have been established pediatric patients 10 years of age and older with HeFH. Use of ATORVALIQ for this indication is based on a double-blind, placebo-controlled clinical trial of atorvastatin in 187 pediatric patients 10 years of age and older with HeFH [see Clinical Studies (14)]. In this limited controlled trial, there was no significant effect on growth or sexual maturation in the boys or girls, or on menstrual cycle length in girls.

The safety and effectiveness of ATORVALIQ as an adjunct to other LDL-C-lowering therapies to reduce LDL-C have been established pediatric patients 10 years of age and older with HoFH. . Use of ATORVALIQ for this indication is based on a trial of atorvastatin without a concurrent control group in 8 pediatric patients 10 years of age and older with HoFH [see Clinical Studies (14)].

The safety and effectiveness of ATORVALIQ have not been established in pediatric patients younger than 10 years of age with HeFH or HoFH, or in pediatric patients with other types of hyperlipidemia (other than HeFH or HoFH).

8.5 Geriatric Use

Of the total number of atorvastatin-treated patients in clinical trials, 15,813 (40%) were ≥65 years old and 2,800 (7%) were ≥75 years old. No overall differences in safety or effectiveness were observed between these patients and younger patients.

Advanced age (≥65 years) is a risk factor for atorvastatin-associated myopathy and rhabdomyolysis. Dose selection for an elderly patient should be cautious, recognizing the greater frequency of decreased hepatic, renal, or cardiac function, and of concomitant disease or other drug therapy and the higher risk of myopathy. Monitor geriatric patients receiving ATORVALIQ for the increased risk of myopathy [see Warnings and Precautions (5.1) and Clinical Pharmacology (12.3)].

8.6 Renal Impairment

Renal impairment is a risk factor for myopathy and rhabdomyolysis. Monitor all patients with renal impairment for development of myopathy. Renal impairment does not affect the plasma concentrations of ATORVALIQ, therefore there is no dosage adjustment in patients with renal impairment [see Warnings and Precautions (5.1) and Clinical Pharmacology (12.3)].

8.7 Hepatic Impairment

In patients with chronic alcoholic liver disease, plasma concentrations of ATORVALIQ are markedly increased. Cmax and AUC are each 4-fold greater in patients with Childs-Pugh A disease. Cmax and AUC are approximately 16-fold and 11-fold increased, respectively, in patients with Childs-Pugh B disease. ATORVALIQ is contraindicated in patients with acute liver failure or decompensated cirrhosis [see Contraindications (4)].

10 OVERDOSAGE

No specific antidotes for ATORVALIQ are known. Contact Poison Control (1-800-222-1222) for latest recommendations. Due to extensive drug binding to plasma proteins, hemodialysis is not expected to significantly enhance ATORVALIQ clearance.

11 DESCRIPTION

ATORVALIQ (atorvastatin) is an inhibitor of 3-hydroxy-3-methylglutaryl-coenzyme A (HMG-CoA) reductase.

Atorvastatin calcium is [R-(R*, R*)]-2-(4-fluorophenyl)-ß, δ-dihydroxy-5-(1-methylethyl)-3-phenyl-4-[(phenylamino)carbonyl]-1H-pyrrole-1-heptanoic acid, calcium salt (2:1) trihydrate. The empirical formula of atorvastatin calcium is (C33H34 FN2O5)2Ca∙3H2O and its molecular weight is 1209.42. Its structural formula is:

Atorvastatin calcium is a white to off-white crystalline powder that is insoluble in aqueous solutions of pH 4 and below. Atorvastatin calcium is very slightly soluble in distilled water, pH 7.4 phosphate buffer, and acetonitrile; slightly soluble in ethanol; and freely soluble in methanol.

ATORVALIQ oral suspension contains 20 mg/5 mL of atorvastatin and the following inactive ingredients: caroboxymethylcellulose sodium, magnesium aluminum silicate, methylparaben, ethylparaben, propylparaben, sucralose, acesulfame potassium, orange flavor, water.

12 CLINICAL PHARMACOLOGY

12.1 Mechanism of Action

Atorvastatin is a selective, competitive inhibitor of HMG-CoA reductase, the rate-limiting enzyme that converts 3-hydroxy-3-methylglutaryl-coenzyme A to mevalonate, a precursor of sterols, including cholesterol. In animal models, atorvastatin lowers plasma cholesterol and lipoprotein levels by inhibiting HMG-CoA reductase and cholesterol synthesis in the liver and by increasing the number of hepatic LDL receptors on the cell surface to enhance uptake and catabolism of LDL; atorvastatin also reduces LDL production and the number of LDL particles.

12.2 Pharmacodynamics

Atorvastatin, as well as some of its metabolites, are pharmacologically active in humans. The liver is the primary site of action and the principal site of cholesterol synthesis and LDL clearance. Drug dosage, rather than systemic drug concentration, correlates better with LDL-C reduction. Individualization of drug dosage should be based on therapeutic response [see Dosage and Administration (2)].

12.3 Pharmacokinetics

Absorption

Atorvastatin is rapidly absorbed after oral administration; maximum plasma concentrations occur within 1 to 2 hours. Extent of absorption increases in proportion to ATORVALIQ dose. The absolute bioavailability of atorvastatin (parent drug) is approximately 14% and the systemic availability of HMG-CoA reductase inhibitory activity is approximately 30%. The low systemic availability is attributed to presystemic clearance in gastrointestinal mucosa and/or hepatic first-pass metabolism. Administration of ATORVALIQ with high fat meal resulted in a 30% and 63% decrease in atorvastatin AUC and Cmax, respectively compared with what was observed in the fasted state. The decrease in exposure can be clinically significant, and therefore ATORVALIQ should be taken only on an empty stomach (1 hour before or 2 hours after a meal)..

Plasma atorvastatin concentrations are lower (approximately 30% for Cmax and AUC) following evening drug administration compared with morning. However, LDL-C reduction is the same regardless of the time of day of drug administration.

Distribution

Mean volume of distribution of atorvastatin is approximately 381 liters. Atorvastatin is ≥98% bound to plasma proteins. A blood/plasma ratio of approximately 0.25 indicates poor drug penetration into red blood cells.

Elimination

Metabolism

Atorvastatin is extensively metabolized to ortho- and parahydroxylated derivatives and various beta-oxidation products. In vitro inhibition of HMG-CoA reductase by ortho- and parahydroxylated metabolites is equivalent to that of atorvastatin. Approximately 70% of circulating inhibitory activity for HMG-CoA reductase is attributed to active metabolites. In vitro studies suggest the importance of atorvastatin metabolism by cytochrome P450 3A4, consistent with increased plasma concentrations of atorvastatin in humans following co-administration with erythromycin, a known inhibitor of this isozyme [see Drug Interactions (7.1)]. In animals, the ortho-hydroxy metabolite undergoes further glucuronidation.

Excretion

Atorvastatin and its metabolites are eliminated primarily in bile following hepatic and/or extra-hepatic metabolism; however, the drug does not appear to undergo enterohepatic recirculation. Mean plasma elimination half-life of atorvastatin in humans is approximately 14 hours, but the half-life of inhibitory activity for HMG-CoA reductase is 20 to 30 hours due to the contribution of active metabolites. Less than 2% of a dose of atorvastatin is recovered in urine following oral administration.

Specific Populations

Geriatric

Plasma concentrations of atorvastatin are higher (approximately 40% for Cmax and 30% for AUC) in healthy elderly subjects (age ≥65 years) than in young adults.

Pediatric

Apparent oral clearance of atorvastatin in pediatric subjects appeared similar to that of adults when scaled allometrically by body weight as the body weight was the only significant covariate in atorvastatin population PK model with data including pediatric HeFH patients (ages 10 years to 17 years of age, n=29) in an open-label, 8-week study.

Gender

Plasma concentrations of atorvastatin in women differ from those in men (approximately 20% higher for Cmax and 10% lower for AUC); however, there is no clinically significant difference in LDL-C reduction with ATORVALIQ between men and women.

Renal Impairment

Renal disease has no influence on the plasma concentrations or LDL-C reduction of ATORVALIQ [see Use in Specific Populations (8.6)].

While studies have not been conducted in patients with end-stage renal disease, hemodialysis is not expected to significantly enhance clearance of atorvastatin since the drug is extensively bound to plasma proteins.

Hepatic Impairment

In patients with chronic alcoholic liver disease, plasma concentrations of atorvastatin are markedly increased. Cmax and AUC are each 4-fold greater in patients with Childs-Pugh A disease. Cmax and AUC are approximately 16-fold and 11-fold increased, respectively, in patients with Childs-Pugh B disease [see Use in Specific Populations (8.7)].

Drug Interactions

Atorvastatin is a substrate of the hepatic transporters, OATP1B1 and OATP1B3 transporter. Metabolites of atorvastatin are substrates of OATP1B1. Atorvastatin is also identified as a substrate of the efflux transporter BCRP, which may limit the intestinal absorption and biliary clearance of atorvastatin.

Table 5: Effect of Co-administered Drugs on the Pharmacokinetics of Atorvastatin
Co-administered drug and dosing regimen | Atorvastatin
 | Dose (mg) | Ratio of AUC [Represents ratio of treatments (co-administered drug plus atorvastatin vs. atorvastatin alone).] | Ratio of Cmax
[See Sections 5.1 and 7 for clinical significance.] Cyclosporine 5.2 mg/kg/day, stable dose | 10 mg QD [Once daily] for 28 days | 8.69 | 10.66
Tipranavir 500 mg BID [Twice daily] /ritonavir 200 mg BID, 7 days | 10 mg SD [Single dose] | 9.36 | 8.58
Glecaprevir 400 mg QD/pibrentasvir 120 mg QD, 7 days | 10 mg QD for 7 days | 8.28 | 22.00
Telaprevir 750 mg q8h [Every 8 hours] , 10 days | 20 mg SD | 7.88 | 10.60
, [The dose of saquinavir plus ritonavir in this study is not the clinically used dose. The increase in atorvastatin exposure when used clinically is likely to be higher than what was observed in this study. Therefore, caution should be applied and the lowest dose necessary should be used.] Saquinavir 400 mg BID/ritonavir 400 mg BID, 15 days | 40 mg QD for 4 days | 3.93 | 4.31
Elbasvir 50 mg QD/grazoprevir 200 mg QD, 13 days | 10 mg SD | 1.94 | 4.34
Simeprevir 150 mg QD, 10 days | 40 mg SD | 2.12 | 1.70
Clarithromycin 500 mg BID, 9 days | 80 mg QD for 8 days | 4.54 | 5.38
Darunavir 300 mg BID/ritonavir 100 mg BID, 9 days | 10 mg QD for 4 days | 3.45 | 2.25
Itraconazole 200 mg QD, 4 days | 40 mg SD | 3.32 | 1.20
Letermovir 480 mg QD, 10 days | 20 mg SD | 3.29 | 2.17
Fosamprenavir 700 mg BID/ritonavir 100 mg BID, 14 days | 10 mg QD for 4 days | 2.53 | 2.84
Fosamprenavir 1400 mg BID, 14 days | 10 mg QD for 4 days | 2.3 | 4.04
Nelfinavir 1250 mg BID, 14 days | 10 mg QD for 28 days | 1.74 | 2.22
Grapefruit Juice, 240 mL QD, [Greater increases in AUC (ratio of AUC up to 2.5) and/or Cmax (ratio of Cmax up to 1.71) have been reported with excessive grapefruit consumption (≥ 750 mL-1.2 liters per day).] | 40 mg SD | 1.37 | 1.16
Diltiazem 240 mg QD, 28 days | 40 mg SD | 1.51 | 1.00
Erythromycin 500 mg QID [Four times daily] , 7 days | 10 mg SD | 1.33 | 1.38
Amlodipine 10 mg, single dose | 80 mg SD | 1.18 | 0.91
Cimetidine 300 mg QID, 2 weeks | 10 mg QDfor 2 weeks | 1.00 | 0.89
Colestipol 10 g BID, 24 weeks | 40 mg QD for 8 weeks | NA | 0.74 [Ratio based on a single sample taken 8-16 h post dose.]
Maalox TC® 30 mL QID, 17 days | 10 mg QD for 15 days | 0.66 | 0.67
Efavirenz 600 mg QD, 14 days | 10 mg for 3 days | 0.59 | 1.01
Rifampin 600 mg QD, 7 days (co‑administered) [Due to the dual interaction mechanism of rifampin, simultaneous co-administration of atorvastatin with rifampin is recommended, as delayed administration of atorvastatin after administration of rifampin has been associated with a significant reduction in atorvastatin plasma concentrations.] | 40 mg SD | 1.12 | 2.90
Rifampin 600 mg QD, 5 days (doses separated) | 40 mg SD | 0.20 | 0.60
Gemfibrozil 600 mg BID, 7 days | 40 mg SD | 1.35 | 1.00
Fenofibrate 160 mg QD, 7 days | 40 mg SD | 1.03 | 1.02
Boceprevir 800 mg TID [Three times daily] , 7 days | 40 mg SD | 2.32 | 2.66

Table 6: Effect of Atorvastatin on the Pharmacokinetics of Co-administered Drugs
Atorvastatin | Co-administered drug and dosing regimen
 | Drug/Dose (mg) | Ratio of AUC | Ratio of Cmax
80 mg QD [Once daily] for 15 days | Antipyrine, 600 mg SD [Single dose] | 1.03 | 0.89
80 mg QD for 10 days | [See Section 7 for clinical significance.] Digoxin 0.25 mg QD, 20 days | 1.15 | 1.20
40 mg QD for 22 days | Oral contraceptive QD, 2 months; - norethindrone 1 mg; - ethinyl estradiol 35 µg | 1.28; 1.19 | 1.23; 1.30
10 mg SD | Tipranavir 500 mg BID [Twice daily] /ritonavir 200 mg BID, 7 days | 1.08 | 0.96
10 mg QD for 4 days | Fosamprenavir 1400 mg BID, 14 days | 0.73 | 0.82
10 mg QD for 4 days | Fosamprenavir 700 mg BID/ritonavir 100 mg BID, 14 days | 0.99 | 0.94

Atorvastatin had no clinically significant effect on prothrombin time when administered to patients receiving chronic warfarin treatment.

13 NONCLINICAL TOXICOLOGY

13.1 Carcinogenesis, Mutagenesis, Impairment of Fertility

In a 2-year carcinogenicity study in rats at dose levels of 10, 30, and 100 mg/kg/day, 2 rare tumors were found in muscle in high-dose females: in one, there was a rhabdomyosarcoma and, in another, there was a fibrosarcoma. This dose represents a plasma AUC (0–24) value of approximately 16 times the mean human plasma drug exposure after an 80 mg oral dose.

A 2-year carcinogenicity study in mice given 100, 200, or 400 mg/kg/day resulted in a significant increase in liver adenomas in high-dose males and liver carcinomas in high-dose females. These findings occurred at plasma AUC (0–24) values of approximately 6 times the mean human plasma drug exposure after an 80 mg oral dose.

In vitro, atorvastatin was not mutagenic or clastogenic in the following tests with and without metabolic activation: the Ames test with Salmonella typhimurium and Escherichia coli, the HGPRT forward mutation assay in Chinese hamster lung cells, and the chromosomal aberration assay in Chinese hamster lung cells. Atorvastatin was negative in the in vivo mouse micronucleus test.

In female rats, atorvastatin at doses up to 225 mg/kg (56 times the human exposure) did not cause adverse effects on fertility. Studies in male rats performed at doses up to 175 mg/kg (15 times the human exposure) produced no changes in fertility. There was aplasia and aspermia in the epididymis of 2 of 10 rats treated with 100 mg/kg/day of atorvastatin for 3 months (16 times the human AUC at the 80 mg dose); testis weights were significantly lower at 30 and 100 mg/kg and epididymal weight was lower at 100 mg/kg. Male rats given 100 mg/kg/day for 11 weeks prior to mating had decreased sperm motility, spermatid head concentration, and increased abnormal sperm. Atorvastatin caused no adverse effects on semen parameters, or reproductive organ histopathology in dogs given doses of 10, 40, or 120 mg/kg for two years.

14 CLINICAL STUDIES

The effectiveness of ATORVALIQ has been established in adequate and well-controlled trials of atorvastatin calcium tablets, referenced below as “atorvastatin.”

Prevention of Cardiovascular Disease

In the Anglo-Scandinavian Cardiac Outcomes Trial (ASCOT), the effect of atorvastatin on fatal and non-fatal coronary heart disease was assessed in 10,305 patients with hypertension, 40-80 years of age (mean of 63 years; 19% women; 95% White, 3% Black, 1% South Asian, 1% other), without a previous myocardial infarction and with total cholesterol (TC) levels ≤251 mg/dL. Additionally, all patients had at least 3 of the following cardiovascular risk factors: male gender (81%), age >55 years (85%), smoking (33%), diabetes (24%), history of CHD in a first-degree relative (26%), TC:HDL >6 (14%), peripheral vascular disease (5%), left ventricular hypertrophy (14%), prior cerebrovascular event (10%), specific ECG abnormality (14%), proteinuria/albuminuria (62%). In this double-blind, placebo-controlled trial, patients were treated with anti-hypertensive therapy (goal BP <140/90 mm Hg for patients without diabetes; <130/80 mm Hg for patients with diabetes) and allocated to either atorvastatin 10 mg daily (n=5168) or placebo (n=5137), using a covariate adaptive method which took into account the distribution of nine baseline characteristics of patients already enrolled and minimized the imbalance of those characteristics across the groups. Patients were followed for a median duration of 3.3 years.

The effect of 10 mg/day of atorvastatin on lipid levels was similar to that seen in previous clinical trials.

Atorvastatin significantly reduced the rate of coronary events [either fatal coronary heart disease (46 events in the placebo group vs. 40 events in the atorvastatin group) or non-fatal MI (108 events in the placebo group vs. 60 events in the atorvastatin group)] with a relative risk reduction of 36% [(based on incidences of 1.9% for atorvastatin vs. 3.0% for placebo), p=0.0005 (see Figure 1)]. The risk reduction was consistent regardless of age, smoking status, obesity, or presence of renal dysfunction. The effect of atorvastatin was seen regardless of baseline LDL levels.

Figure 1: Effect of Atorvastatin 10 mg/day on Cumulative Incidence of Non-Fatal Myocardial Infarction or Coronary Heart Disease Death (in ASCOT-LLA)

Atorvastatin also significantly decreased the relative risk for revascularization procedures by 42% (incidences of 1.4% for atorvastatin and 2.5% for placebo). Although the reduction of fatal and non-fatal strokes did not reach a pre-defined significance level (p=0.01), a favorable trend was observed with a 26% relative risk reduction (incidences of 1.7% for atorvastatin and 2.3% for placebo). There was no significant difference between the treatment groups for death due to cardiovascular causes (p=0.51) or noncardiovascular causes (p=0.17).

In the Collaborative Atorvastatin Diabetes Study (CARDS), the effect of atorvastatin on cardiovascular disease (CVD) endpoints was assessed in 2838 subjects (94% White, 2% Black, 2% South Asian, 1% other; 68% male), ages 40-75 with type 2 diabetes based on WHO criteria, without prior history of cardiovascular disease and with LDL ≤160 mg/dL and TG ≤600 mg/dL. In addition to diabetes, subjects had 1 or more of the following risk factors: current smoking (23%), hypertension (80%), retinopathy (30%), or microalbuminuria (9%) or macroalbuminuria (3%). No subjects on hemodialysis were enrolled in the trial. In this multicenter, placebo-controlled, double-blind clinical trial, subjects were randomly allocated to either atorvastatin 10 mg daily (1429) or placebo (1411) in a 1:1 ratio and were followed for a median duration of 3.9 years. The primary endpoint was the occurrence of any of the major cardiovascular events: myocardial infarction, acute CHD death, unstable angina, coronary revascularization, or stroke. The primary analysis was the time to first occurrence of the primary endpoint.

Baseline characteristics of subjects were: mean age of 62 years, mean HbA1c 7.7%; median LDL-C 120 mg/dL; median TC 207 mg/dL; median TG 151 mg/dL; median HDL-C 52 mg/dL.

The effect of atorvastatin 10 mg/day on lipid levels was similar to that seen in previous clinical trials.

Atorvastatin significantly reduced the rate of major cardiovascular events (primary endpoint events) (83 events in the atorvastatin group vs. 127 events in the placebo group) with a relative risk reduction of 37%, HR 0.63, 95% CI (0.48, 0.83) (p=0.001) (see Figure 2). An effect of atorvastatin was seen regardless of age, sex, or baseline lipid levels.

Atorvastatin significantly reduced the risk of stroke by 48% (21 events in the atorvastatin group vs. 39 events in the placebo group), HR 0.52, 95% CI (0.31, 0.89) (p=0.016) and reduced the risk of MI by 42% (38 events in the atorvastatin group vs. 64 events in the placebo group), HR 0.58, 95.1% CI (0.39, 0.86) (p=0.007). There was no significant difference between the treatment groups for angina, revascularization procedures, and acute CHD death.

There were 61 deaths in the atorvastatin group vs. 82 deaths in the placebo group (HR 0.73, p=0.059).

Figure 2: Effect of Atorvastatin 10 mg/day on Time to Occurrence of Major Cardiovascular Event (myocardial infarction, acute CHD death, unstable angina, coronary revascularization, or stroke) in CARDS

In the Treating to New Targets Study (TNT), the effect of atorvastatin 80 mg/day vs. atorvastatin 10 mg/day on the reduction in cardiovascular events was assessed in 10,001 subjects (94% White, 81% male, 38% ≥65 years) with clinically evident coronary heart disease who had achieved a target LDL-C level <130 mg/dL after completing an 8-week, open-label, run-in period with atorvastatin 10 mg/day. Subjects were randomly assigned to either 10 mg/day or 80 mg/day of atorvastatin and followed for a median duration of 4.9 years. The primary endpoint was the time-to-first occurrence of any of the following major cardiovascular events (MCVE): death due to CHD, non-fatal myocardial infarction, resuscitated cardiac arrest, and fatal and non-fatal stroke. The mean LDL-C, TC, TG, non-HDL, and HDL cholesterol levels at 12 weeks were 73, 145, 128, 98, and 47 mg/dL during treatment with 80 mg of atorvastatin and 99, 177, 152, 129, and 48 mg/dL during treatment with 10 mg of atorvastatin.

Treatment with atorvastatin 80 mg/day significantly reduced the rate of MCVE (434 events in the 80 mg/day group vs. 548 events in the 10 mg/day group) with a relative risk reduction of 22%, HR 0.78, 95% CI (0.69, 0.89), p=0.0002 (see Figure 3 and Table 7). The overall risk reduction was consistent regardless of age (<65, ≥65) or sex.

Figure 3: Effect of Atorvastatin 80 mg/day vs. 10 mg/day on Time to Occurrence of Major Cardiovascular Events (TNT)

Table 7: Overview of Efficacy Results in TNT
Endpoint | Atorvastatin; 10 mg; (N=5006) |  | Atorvastatin; 80 mg; (N=4995) |  | HR [Atorvastatin 80 mg: atorvastatin 10 mg] (95%CI)
PRIMARY ENDPOINT | n | (%) | n | (%)
First major cardiovascular endpoint | 548 | (10.9) | 434 | (8.7) | 0.78 (0.69, 0.89)
Components of the Primary Endpoint
CHD death | 127 | (2.5) | 101 | (2.0) | 0.80 (0.61, 1.03)
Non-fatal, non-procedure related MI | 308 | (6.2) | 243 | (4.9) | 0.78 (0.66, 0.93)
Resuscitated cardiac arrest | 26 | (0.5) | 25 | (0.5) | 0.96 (0.56, 1.67)
Stroke (fatal and non-fatal) | 155 | (3.1) | 117 | (2.3) | 0.75 (0.59, 0.96)
SECONDARY ENDPOINTS [Secondary endpoints not included in primary endpoint]
First CHF with hospitalization | 164 | (3.3) | 122 | (2.4) | 0.74 (0.59, 0.94)
First PVD endpoint | 282 | (5.6) | 275 | (5.5) | 0.97 (0.83, 1.15)
First CABG or other coronary revascularization procedure [Component of other secondary endpoints] | 904 | (18.1) | 667 | (13.4) | 0.72 (0.65, 0.80)
First documented angina endpoint | 615 | (12.3) | 545 | (10.9) | 0.88 (0.79, 0.99)
All-cause mortality | 282 | (5.6) | 284 | (5.7) | 1.01 (0.85, 1.19)
Components of All-Cause Mortality
Cardiovascular death | 155 | (3.1) | 126 | (2.5) | 0.81 (0.64, 1.03)
Noncardiovascular death | 127 | (2.5) | 158 | (3.2) | 1.25 (0.99, 1.57)
Cancer death | 75 | (1.5) | 85 | (1.7) | 1.13 (0.83, 1.55)
Other non-CV death | 43 | (0.9) | 58 | (1.2) | 1.35 (0.91, 2.00)
Suicide, homicide, and other traumatic non-CV death | 9 | (0.2) | 15 | (0.3) | 1.67 (0.73, 3.82)

HR=hazard ratio; CHD=coronary heart disease; CI=confidence interval; MI=myocardial infarction; CHF=congestive heart failure; CV=cardiovascular; PVD=peripheral vascular disease; CABG=coronary artery bypass graft

Confidence intervals for the Secondary Endpoints were not adjusted for multiple comparisons

Of the events that comprised the primary efficacy endpoint, treatment with atorvastatin 80 mg/day significantly reduced the rate of non-fatal, non-procedure related MI and fatal and non-fatal stroke, but not CHD death or resuscitated cardiac arrest (Table 7). Of the predefined secondary endpoints, treatment with atorvastatin 80 mg/day significantly reduced the rate of coronary revascularization, angina, and hospitalization for heart failure, but not peripheral vascular disease. The reduction in the rate of CHF with hospitalization was only observed in the 8% of patients with a prior history of CHF.

There was no significant difference between the treatment groups for all-cause mortality (Table 7). The proportions of subjects who experienced cardiovascular death, including the components of CHD death and fatal stroke, were numerically smaller in the atorvastatin 80 mg group than in the atorvastatin 10 mg treatment group. The proportions of subjects who experienced noncardiovascular death were numerically larger in the atorvastatin 80 mg group than in the atorvastatin 10 mg treatment group.

Primary Hyperlipidemia in Adults

Atorvastatin reduces total-C, LDL-C, apo B, and TG, and increases HDL-C in patients with hyperlipidemia (heterozygous familial and nonfamilial) and mixed dyslipidemia. Therapeutic response is seen within 2 weeks, and maximum response is usually achieved within 4 weeks and maintained during chronic therapy.

In two multicenter, placebo-controlled, dose-response trials in patients with hyperlipidemia, atorvastatin given as a single dose over 6 weeks, significantly reduced total-C, LDL-C, apo B, and TG. (Pooled results are provided in Table 8.)

Table 8: Dose Response in Patients with Primary Hyperlipidemia (Adjusted Mean % Change From Baseline) [Results are pooled from 2 dose-response trials.]
Dose | N | TC | LDL‑C | Apo B | TG | HDL‑C
Placebo | 21 | 4 | 4 | 3 | 10 | -3
10 | 22 | -29 | -39 | -32 | -19 | 6
20 | 20 | -33 | -43 | -35 | -26 | 9
40 | 21 | -37 | -50 | -42 | -29 | 6
80 | 23 | -45 | -60 | -50 | -37 | 5

In three multicenter, double-blind trials in patients with hyperlipidemia, atorvastatin was compared to other statins. After randomization, patients were treated for 16 weeks with either atorvastatin 10 mg per day or a fixed dose of the comparative agent (Table 9).

Table 9: Mean Percentage Change From Baseline at Endpoint (Double-Blind, Randomized, Active-Controlled Trials)
Treatment; (Daily Dose) | N | Total‑C | LDL‑C | Apo B | TG | HDL‑C
Trial 1
Atorvastatin 10 mg | 707 | -27 [Significantly different from lovastatin, ANCOVA, p ≤0.05] | -36 | -28 | -17 | +7
Lovastatin 20 mg | 191 | -19 | -27 | -20 | -6 | +7
95% CI for Diff [A negative value for the 95% CI for the difference between treatments favors atorvastatin for all except HDL-C, for which a positive value favors atorvastatin. If the range does not include 0, this indicates a statistically significant difference.] |  | -9.2, -6.5 | -10.7, -7.1 | -10.0, -6.5 | -15.2, -7.1 | -1.7, 2.0
Trial 2
Atorvastatin 10 mg | 222 | -25 [Significantly different from pravastatin, ANCOVA, p ≤0.05] | -35 | -27 | -17 | +6
Pravastatin 20 mg | 77 | -17 | -23 | -17 | -9 | +8
95% CI for Diff |  | -10.8, -6.1 | -14.5, -8.2 | -13.4, -7.4 | -14.1, -0.7 | -4.9, 1.6
Trial 3
Atorvastatin 10 mg | 132 | -29 [Significantly different from simvastatin, ANCOVA, p ≤0.05] | -37 | -34 | -23 | +7
Simvastatin 10 mg | 45 | -24 | -30 | -30 | -15 | +7
95% CI for Diff |  | -8.7, -2.7 | -10.1, -2.6 | -8.0, -1.1 | -15.1, -0.7 | -4.3, 3.9

Table 9 does not contain data comparing the effects of atorvastatin 10 mg and higher doses of lovastatin, pravastatin, and simvastatin. The drugs compared in the trials summarized in the table are not necessarily interchangeable.

Hypertriglyceridemia in Adults

The response to atorvastatin in 64 patients with isolated hypertriglyceridemia treated across several clinical trials is shown in the table below (Table 10). For the atorvastatin-treated patients, median (min, max) baseline TG level was 565 (267-1502).

Table 10: Combined Patients with Isolated Elevated TG: Median (min, max) Percentage Change From Baseline
 | Placebo; (N=12) | Atorvastatin 10 mg; (N=37) | Atorvastatin 20 mg; (N=13) | Atorvastatin 80 mg; (N=14)
Triglycerides | -12.4 (-36.6, 82.7) | -41.0 (-76.2, 49.4) | -38.7 (-62.7, 29.5) | -51.8 (-82.8, 41.3)
Total-C | -2.3 (-15.5, 24.4) | -28.2 (-44.9, -6.8) | -34.9 (-49.6, -15.2) | -44.4 (-63.5, -3.8)
LDL-C | 3.6 (-31.3, 31.6) | -26.5 (-57.7, 9.8) | -30.4 (-53.9, 0.3) | -40.5 (-60.6, -13.8)
HDL-C | 3.8 (-18.6, 13.4) | 13.8 (-9.7, 61.5) | 11.0 (-3.2, 25.2) | 7.5 (-10.8, 37.2)
non-HDL-C | -2.8 (-17.6, 30.0) | -33.0 (-52.1, -13.3) | -42.7 (-53.7, -17.4) | -51.5 (-72.9, -4.3)

Dysbetalipoproteinemia in Adults

The results of an open-label crossover trial of 16 patients (genotypes: 14 apo E2/E2 and 2 apo E3/E2) with dysbetalipoproteinemia are shown in the table below (Table 11).

Table 11: Open-Label Crossover Trial of 16 Patients with Dysbetalipoproteinemia
 |  | Median % Change (min, max)
 | Median (min, max) at Baseline (mg/dL) | Atorvastatin; 10 mg | Atorvastatin; 80 mg
Total-C | 442 (225, 1320) | -37 (-85, 17) | -58 (-90, -31)
Triglycerides | 678 (273, 5990) | -39 (-92, -8) | -53 (-95, -30)
IDL-C + VLDL-C | 215 (111, 613) | -32 (-76, 9) | -63 (-90, -8)
non-HDL-C | 411 (218, 1272) | -43 (-87, -19) | -64 (-92, -36)

HoFH in Adults and Pediatric Patients

In a trial without a concurrent control group, 29 patients (mean age of 22 years, median age of 24 years, 31% <18 years) with HoFH received maximum daily doses of 20 to 80 mg of atorvastatin. The mean LDL-C reduction in this trial was 18%. Twenty-five patients with a reduction in LDL-C had a mean response of 20% (range of 7% to 53%, median of 24%); the remaining 4 patients had 7% to 24% increases in LDL-C. Five of the 29 patients had absent LDL-receptor function. Of these, 2 patients also had a portacaval shunt and had no significant reduction in LDL-C. The remaining 3 receptor-negative patients had a mean LDL-C reduction of 22%.

HeFH in Pediatric Patients

In a double-blind, placebo-controlled trial followed by an open-label phase, 187 boys and post-menarchal girls 10 years to 17 years of age (mean age 14.1 years; 31% female; 92% White, 1.6% Blacks, 1.6% Asians, 4.8% other) with heterozygous familial hypercholesterolemia (HeFH) or severe hypercholesterolemia, were randomized to atorvastatin (n=140) or placebo (n=47) for 26 weeks and then all received atorvastatin for 26 weeks. Inclusion in the trial required 1) a baseline LDL-C level ≥ 190 mg/dL or 2) a baseline LDL-C level ≥ 160 mg/dL and positive family history of FH or documented premature cardiovascular disease in a first or second-degree relative. The mean baseline LDL-C value was 219 mg/dL (range: 139-385 mg/dL) in the atorvastatin group compared to 230 mg/dL (range: 160-325 mg/dL) in the placebo group. The dosage of atorvastatin (once daily) was 10 mg for the first 4 weeks and uptitrated to 20 mg if the LDL-C level was >130 mg/dL. The number of atorvastatin-treated patients who required uptitration to 20 mg after Week 4 during the double-blind phase was 78 (56%).

Atorvastatin significantly decreased plasma levels of total-C, LDL-C, triglycerides, and apolipoprotein B during the 26-week double‑blind phase (see Table 12).

Table 12: Lipid-altering Effects of Atorvastatin in Adolescent Boys and Girls with Heterozygous Familial Hypercholesterolemia or Severe Hypercholesterolemia (Mean Percentage Change From Baseline at Endpoint in Intention‑to‑Treat Population)
DOSAGE | N | Total-C | LDL-C | HDL-C | TG | Apolipoprotein B
Placebo | 47 | -1.5 | -0.4 | -1.9 | 1.0 | 0.7
Atorvastatin | 140 | -31.4 | -39.6 | 2.8 | -12.0 | -34.0

The mean achieved LDL-C value was 130.7 mg/dL (range: 70.0-242.0 mg/dL) in the atorvastatin group compared to 228.5 mg/dL (range: 152.0-385.0 mg/dL) in the placebo group during the 26-week double-blind phase.

Atorvastatin was also studied in a three year open-label, uncontrolled trial that included 163 patients with HeFH who were 10 years to 15 years old (82 boys and 81 girls). All patients had a clinical diagnosis of HeFH confirmed by genetic analysis (if not already confirmed by family history). Approximately 98% were White, and less than 1% were Black or Asian. Mean LDL-C at baseline was 232 mg/dL. The starting atorvastatin dosage was 10 mg once daily and doses were adjusted to achieve a target of <130 mg/dL LDL-C. The reductions in LDL-C from baseline were generally consistent across age groups within the trial as well as with previous clinical trials in both adult and pediatric placebo-controlled trials.

16 HOW SUPPLIED/STORAGE AND HANDLING

ATORVALIQ (atorvastatin calcium) oral suspension 20 mg/5 mL is supplied in amber glass bottles with a child-resistant closure.

Each bottle (NDC 46287-030-01) contains 150 mL of atorvastatin calcium oral suspension 20 mg/5 mL.

Storage

Store at 20° C – 25° C (68° F–77° F); excursions permitted to 15° C to 30° C (59° F to 86° F). [See USP Controlled Room Temperature].

Store and dispense ATORVALIQ in its original bottle. Use within 60 days of first opening the bottle, then discard any remainder.

17 PATIENT COUNSELING INFORMATION

Advise the patient to read the FDA-approved patient labeling (Patient Information).

Instruct patients or caregivers to use an oral dosing syringe or oral dosing cup to correctly measure the prescribed amount of medication. Inform patients that oral dosing syringes and cups may be obtained from their pharmacy [see Dosage and Administration (2.1)].

Myopathy and Rhabdomyolysis

Advise patients that ATORVALIQ may cause myopathy and rhabdomyolysis. Inform patients that the risk is also increased when taking certain types of medication or consuming large quantities of grapefruit juice and they should discuss all medication, both prescription and over the counter, with their healthcare provider. Instruct patients to promptly report any unexplained muscle pain, tenderness or weakness particularly if accompanied by malaise or fever [see Warnings and Precautions (5.1), Drug Interactions (7.1)].

Hepatic Dysfunction

Inform patients that ATORVALIQ may cause liver enzyme elevations and possibly liver failure. Advise patients to promptly report fatigue, anorexia, right upper abdominal discomfort, dark urine or jaundice [see Warnings and Precautions (5.3)].

Increases in HbA1c and Fasting Serum Glucose Levels

Inform patients that increases in HbA1c and fasting serum glucose levels may occur with ATORVALIQ. Encourage patients to optimize lifestyle measures, including regular exercise, maintaining a healthy body weight, and making healthy food choices [see Warnings and Precautions (5.4)].

Pregnancy

Advise pregnant patients and patients who can become pregnant of the potential risk to a fetus. Advise patients to inform their healthcare provider of a known or suspected pregnancy to discuss if ATORVALIQ should be discontinued [see Use in Specific Populations (8.1)].

Lactation

Advise patients that breastfeeding is not recommended during treatment with ATORVALIQ [see Use in Specific Populations (8.2)].

Missed Dose

Instruct patients to take ATORVALIQ only as prescribed. If a dose is missed, it should be taken as soon as possible. If the dose was missed by more than 12 hours, advise patients not to take the missed dose and resume with the next scheduled dose.

This product’s label may have been updated. For the most recent prescribing information, please visit www.atorvaliq.com.

Distributed by
CMP Pharma Inc.
Farmville, NC 27828

PATIENT INFORMATION

ATORVALIQ (uh-tore-vah-leek)
(atorvastatin calcium)
oral suspension

What is ATORVALIQ?

ATORVALIQ is a prescription medicine that contains a cholesterol lowering medicine (statin) called atorvastatin. ATORVALIQ is used:

- to reduce the risk of:
  - heart attack, stroke, certain types of heart surgery and chest pain in adults who do not have heart disease but have other multiple risk factors for heart disease.
  - heart attack and stroke in adults with type 2 diabetes mellitus who do not have heart disease but have other multiple risk factors.
  - heart attack that does not cause death, stroke, certain types of heart surgery, hospitalization for congestive heart failure, and chest pain in adults with heart disease.
- along with diet to reduce low density lipoprotein cholesterol (LDL-C) or bad cholesterol:
  - in adults with primary hyperlipidemia.
  - in adults and children aged 10 years and older with heterozygous familial hypercholesterolemia (HeFH). This is an inherited condition that causes high levels of bad cholesterol.
- along with other cholesterol lowering treatments or alone if such treatments are unavailable in adults and children aged 10 years and older with homozygous familial hypercholesterolemia (HoFH). This is an inherited condition that causes high levels of bad cholesterol.
- along with diet for the treatment of adults with:
  - primary dysbetalipoproteinemia (an inherited condition that causes high levels of cholesterol and fat).
  - hypertriglyceridemia.

It is not known if ATORVALIQ is safe and effective in children younger than 10 years of age with HeFH or HoFH or in children with other types of hyperlipidemias (other than HeFH or HoFH).

Do not take ATORVALIQ if you:

- have liver problems (acute liver failure or decompensated cirrhosis).
- are allergic to atorvastatin or any of the ingredients in ATORVALIQ. Stop using ATORVALIQ and get medical help right away if you have symptoms of a serious allergic reaction including:
  - swelling of your face, lips, tongue or throat
  - problems breathing or swallowing
  - fainting or feeling dizzy
  - very rapid heartbeat
  - severe skin rash or itching
  - flu-like symptoms including fever, sore throat, cough, tiredness, and joint pain

See the end of this Patient Information leaflet for a complete list of ingredients in ATORVALIQ.

Before you take ATORVALIQ, tell your healthcare provider about all of your medical conditions, including if you:

- have unexplained muscle aches or weakness.
- drink more than 2 glasses of alcohol daily.
- have diabetes.
- have thyroid problems.
- have kidney problems.
- had a stroke.
- are pregnant or plan to become pregnant. ATORVALIQ may harm your unborn baby. If you become pregnant, stop taking ATORVALIQ and call your healthcare provider right away.
- are breastfeeding or plan to breastfeed. You and your healthcare provider should decide if you will take ATORVALIQ or breastfeed. You should not do both. Talk to your healthcare provider about the best way to feed your baby if you take ATORVALIQ.

Tell your healthcare provider about all the medicines you take, including prescription and over-the-counter medicines, vitamins, and herbal supplements . ATORVALIQ and certain other medicines can increase the risk of muscle problems or other side effects.

Especially tell your healthcare provider if you take medicines for:

- your immune system (cyclosporine)
- cholesterol (gemfibrozil)
- infections (erythromycin, clarithromycin, itraconazole, ketoconazole, posaconazole, and voriconazole)
- birth control pills
- heart failure (digoxin)
- gout (colchicine)
- niacin
- fibrates
- treating HIV, AIDS, or hepatitis C (anti-virals)

- tipranavir plus ritonavir
- ledipasvir plus sofosbuvir
- saquinavir plus ritonavir
- fosamprenavir
- elbasvir plus grazoprevir
- nelfinavir

- glecaprevir plus pibrentasvir
- simeprevir
- darunavir plus ritonavir
- fosamprenavir plus ritonavir
- letermovir

Ask your healthcare provider or pharmacist for a list of medicines if you are not sure. Know all the medicines you take. Keep a list of them to show your healthcare provider and pharmacist when you get a new medicine.

How should I take ATORVALIQ?

- Take ATORVALIQ exactly as your healthcare provider tells you to take it.
- Do not change your dose or stop ATORVALIQ without talking to your healthcare provider.
- Your healthcare provider may do blood tests to check your cholesterol levels during your treatment with ATORVALIQ. Your dose of ATORVALIQ may be changed based on these blood test results.
- Take ATORVALIQ each day at any time of day. ATORVALIQ should be taken on an empty stomach (1 hour before or 2 hours after a meal).
- Your healthcare provider should start you on a cholesterol lowering diet before giving you ATORVALIQ. Stay on this cholesterol lowering diet when you take ATORVALIQ.
- Use an oral dosing syringe to correctly measure your dose of ATORVALIQ. Ask your pharmacist for an oral dosing syringe if you do not have one.
- If you miss a dose of ATORVALIQ, take it as soon as you remember. Do not take ATORVALIQ if it has been more than 12 hours since you missed your last dose. Wait and take the next dose at your regular time. Do not take 2 doses of ATORVALIQ at the same time.
- If you take too much ATORVALIQ or overdose, call your healthcare provider or Poison Control Center at 1-800-222-1222 or go to the nearest emergency room right away.

What should I avoid while taking ATORVALIQ?

- Avoid drinking more than 1.2 liters of grapefruit juice each day.

What are the possible side effects of ATORVALIQ?

ATORVALIQ may cause serious side effects including:

- Muscle pain, tenderness and weakness (myopathy). Muscle problems, including muscle breakdown, can be serious in some people and, rarely, cause kidney damage that can lead to death.
  Tell your healthcare provider right away if you have:
  - unexplained muscle pain, tenderness, or weakness, especially if you also have a fever or feel more tired than usual while you take ATORVALIQ.
  - muscle problems that do not go away after your healthcare provider has told you to stop taking ATORVALIQ. Your healthcare provider may do further tests to diagnose the cause of your muscle problems.
Your chances of getting muscle problems are higher if you:
  1. are taking certain other medicines while you take ATORVALIQ
  2. drink large amounts of grapefruit juice
  3. are 65 years of age or older
  4. have thyroid problems (hypothyroidism) that are not controlled
  5. have kidney problems
  6. are taking higher doses of ATORVALIQ
- Liver problems. Your healthcare provider should do blood tests to check your liver before you start taking ATORVALIQ and if you have symptoms of liver problems while you take ATORVALIQ. Call your healthcare provider right away if you have the following symptoms of liver problems:
  - feel tired or weak
  - nausea or vomiting
  - loss of appetite
  - upper belly pain
  - dark amber colored urine
  - yellowing of your skin or the whites of your eyes
- Increase in blood sugar level. Your blood sugar level may increase while you are taking ATORVALIQ.
  Exercise regularly and make healthy food choices to maintain healthy body weight.

The most common side effects of ATORVALIQ include:

- nasal congestion, sore throat, runny nose
- diarrhea
- urinary tract infection
- nausea
- muscle spasms
- throat pain

- muscle and joint pain
- pain in extremity
- upset stomach
- musculoskeletal pain
- trouble sleeping

These are not all the possible side effects of ATORVALIQ. For more information, ask you healthcare provider or pharmacist. Call your healthcare provider for medical advice about side effects. You may report side effects to FDA at 1-800-FDA-1088.

How do I store ATORVALIQ?

- Store ATORVALIQ at room temperature between 68°F to 77°F (20°C to 25°C) in the original bottle.
- Throw away (discard) any unused portion of ATORVALIQ in the household trash after 60 days of first opening the bottle.
- Do not keep medicine that is out of date or that you no longer need.
- Keep ATORVALIQ and all medicines out of the reach of children.

General information about the safe and effective use of ATORVALIQ.

Medicines are sometimes prescribed for purposes other than those listed in a Patient Information leaflet. Do not use ATORVALIQ for a condition for which it was not prescribed. Do not give ATORVALIQ to other people, even if they have the same symptoms you have. It may harm them. If you would like more information about ATORVALIQ, talk with your healthcare provider. You can ask your healthcare provider or pharmacist for information about ATORVALIQ that is written for health professionals.

What are the ingredients in ATORVALIQ?

Active Ingredient: atorvastatin calcium

Inactive Ingredients: carboxymethylcellulose sodium, magnesium aluminum silicate, methylparaben, ethylparaben, propylparaben, sucralose, acesulfame potassium, orange flavor, water.

Distributed by:
CMP Pharma Inc.
Farmville, NC 27828 U.S.A

For more information, go to the ATORVALIQ website at www.atorvaliq.com

This Patient Information has been approved by the U.S. Food and Drug Administration Issued: 02/2023

PRINCIPAL DISPLAY PANEL - Bottle Label

NDC 46287-030-01

150 mL

Rx Only

Atorvaliq®

(Atorvastatin Calcium Oral Suspension)

20 mg/5 mL

FOR ORAL USE ONLY. SHAKE WELL BEFORE USE.